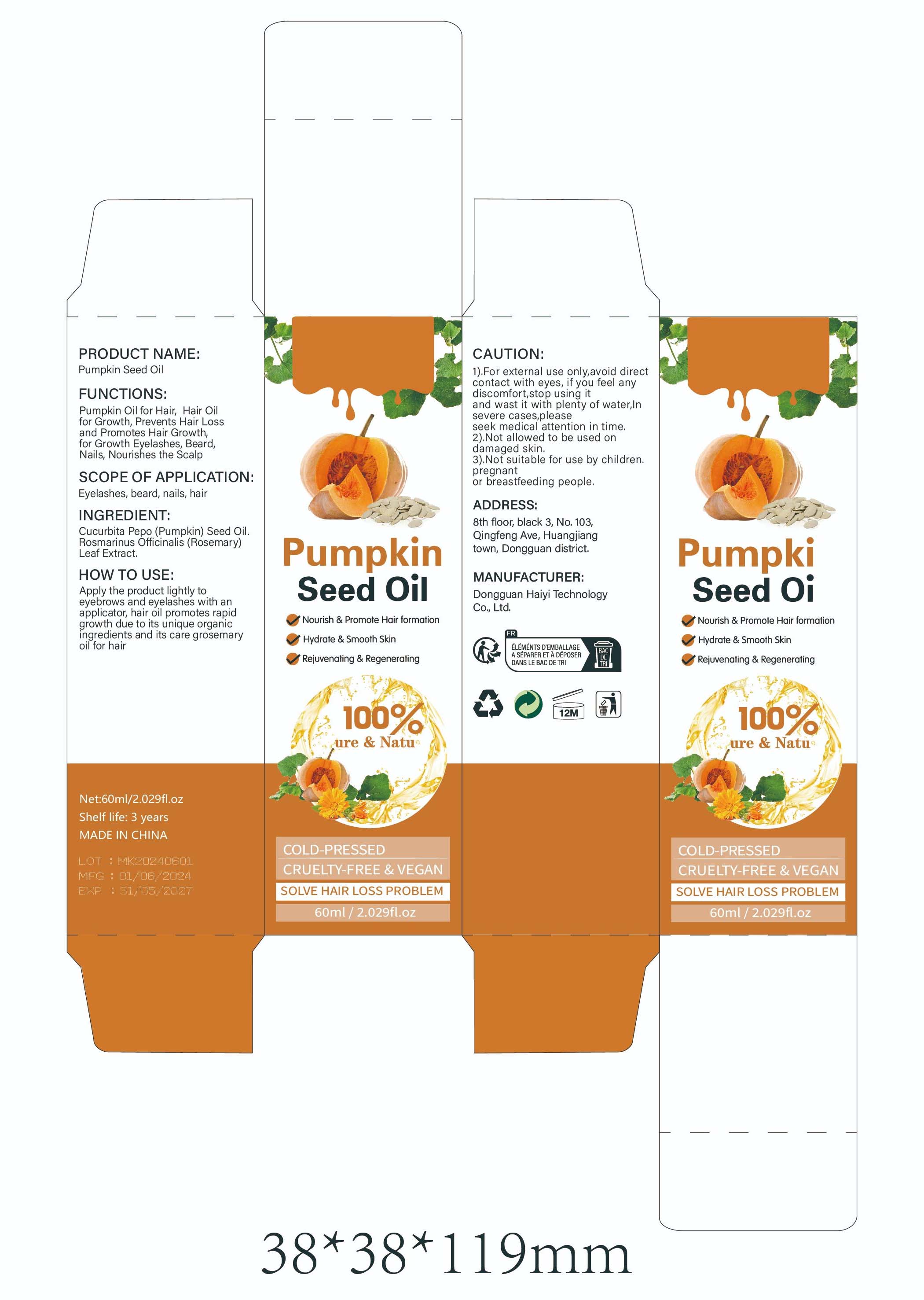 DRUG LABEL: Pumpkin Seed Oil
NDC: 84732-015 | Form: LIQUID
Manufacturer: Dongguan Haiyi Technology Co.,Ltd.
Category: otc | Type: HUMAN OTC DRUG LABEL
Date: 20240925

ACTIVE INGREDIENTS: PUMPKIN SEED OIL 1 mg/60 mL
INACTIVE INGREDIENTS: ROSEMARY

ACTIVE INGREDIENT

Cucurbita Pepo (Pumpkin) Seed Oil

Inactive ingredient

Rosmarinus Officinalis (Rosemarv) Leaf Extract.

Purpose section

Pumpkin Oil for Hair, Hair Oilfor Growth, Prevents Hair Lossand Promotes Hair Growth,for Growth Eyelashes, Beard,Nails, Nourishes the Scalp

stop use

This product may cause allergic reactions in asmall number of people.
lf youexperience any discomfort,please stop using it immediately.

Warning

1).For external use only,avoid directcontact with eyes, if you feel anydiscomfort,stop using itand wast it with plenty of water,Insevere cases,pleaseseek medical attention in time.

2).Not allowed to be used ondamaged skin.

3).Not suitable for use by children.pregnantor breastfeeding people.

not use

Not suitable for use by children, pregnantor breastfeeding people.

OUT OF CHILDREN

KEEP THE PRODUCT OUT OF REACH OF CHILDREN to

HOW TO USE

Apply the product lightly to eyebrows and eyelashes with anapplicator, hair oil promotes rapid growth due to its unique organicingredients and its care grosemaryoil for hair

Dosage

take an appropriateamount,Use 2-3 times a week